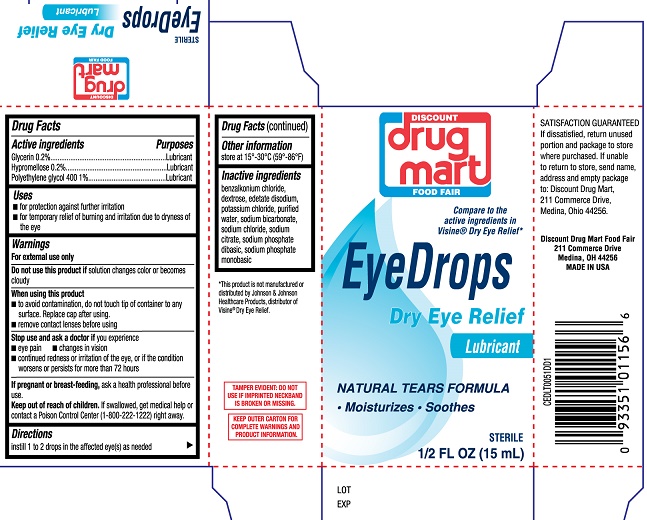 DRUG LABEL: Discount Drug Mart Eye Drops Dry Eye Relief
NDC: 53943-032 | Form: SOLUTION/ DROPS
Manufacturer: Discount Drug Mart
Category: otc | Type: HUMAN OTC DRUG LABEL
Date: 20251230

ACTIVE INGREDIENTS: GLYCERIN 0.2 g/100 mL; HYPROMELLOSE, UNSPECIFIED 0.2 g/100 mL; POLYETHYLENE GLYCOL 400 1 g/100 mL
INACTIVE INGREDIENTS: DEXTROSE; BENZALKONIUM CHLORIDE; EDETATE DISODIUM; POTASSIUM CHLORIDE; WATER; SODIUM BICARBONATE; SODIUM CHLORIDE; SODIUM CITRATE; SODIUM PHOSPHATE, DIBASIC; SODIUM PHOSPHATE, MONOBASIC

Discount Drug Mart Eye Drops Dry Eye Relief 15mL (PLD)

Active ingredients

Glycerin 0.2%

Hypromellose 0.2%

Polyethylene glycol 400 1%

Purpose

Glycerin.....Lubricant

Hypromellose.....Lubricant

Polyethylene glycol 400.....Lubricant

Uses

- for the temporary relief of burning and irritation due to dryness of the eye
- for protection against further irritation

Warnings

For external use only

Do not use this product if solution changes color or becomes cloudy

When using this product

- to avoid contamination, do not touch tip of container to any surface. Replace cap after using.
- remove contact lens before using

Stop use and ask a doctor if you experience

- eye pain
- changes in vision
- continued redness or irritation of the eye, or if the condition worsens or persists for more than 72 hours

PREGNANCY OR BREAST FEEDING

If pregnant or breast-feeding, ask a health professional before use.

Keep out of reach of children If swallowed get medical help or contact a Poison Control Center (1-800-222-1222) right away.

Directions

- Instill 1 or 2 drops in the affected eye(s) as needed

Other information

Store at 15o-30oC (59o-86oF)

Inactive ingredients

benzalkonium chloride, dextrose, edetate disodium, potassium chloride, purified water, sodium bicarbonate, sodium chloride, sodium citrate, sodium phosphate dibasic, sodium phosphate monobasic